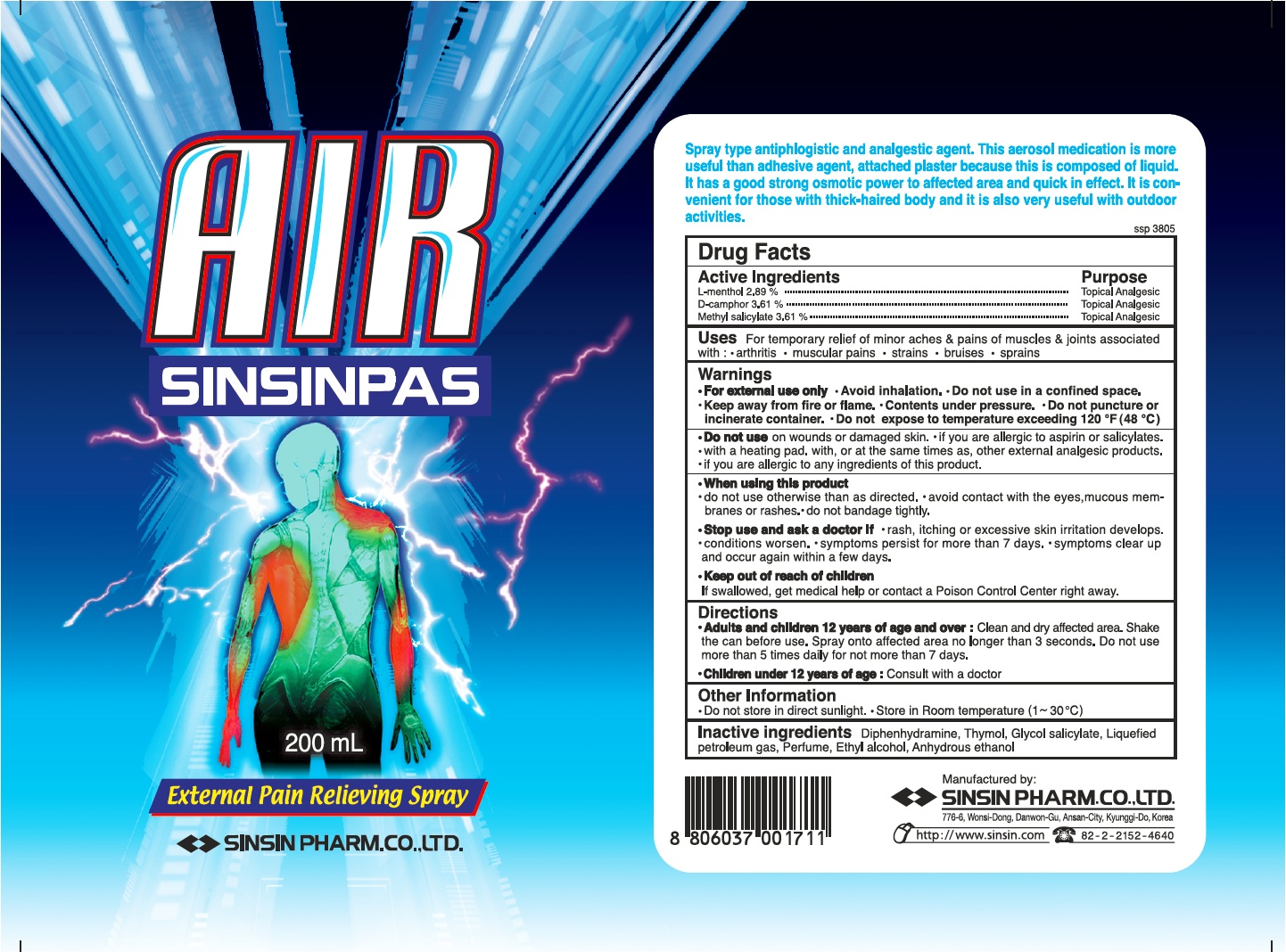 DRUG LABEL: Air Sinsin Pas
NDC: 55264-011 | Form: AEROSOL, SPRAY
Manufacturer: Sinsin Pharmaceutical Co., Ltd.
Category: otc | Type: HUMAN OTC DRUG LABEL
Date: 20110606

ACTIVE INGREDIENTS: CAMPHOR (SYNTHETIC) 0.361 g/100 mL; MENTHOL 0.289 g/100 mL; METHYL SALICYLATE 0.361 g/100 mL
INACTIVE INGREDIENTS: DIPHENHYDRAMINE; THYMOL; GLYCOL SALICYLATE; LIQUEFIED PETROLEUM GAS; ALCOHOL

Drug Facts

Active ingredients

L-menthol 2.89%

D-camphor 3.61%

Methyl salicylate 3.61%

Purpose

Topical Analgesic

Uses

For temporary relief of minor aches and pains of muscles and joints associated with:

- arthritis
- muscular pains
- strains
- bruises
- sprains

Warnings

- For external use only.
- Avoid inhalation.
- Do not use in a confined space.
- Keep away from fire or flame.
- Contents under pressure.
- Do not puncture or incinerate container.
- Do not expose to temperature exceeding 120 degrees F (48 degrees C).

Do not use

- on wounds or damaged skin.
- if you are allergic to aspirin or salicylates.
- with a heating pad, with, or at the same times as, other external analegic products.
- if you are allergic to any ingredients of this product.

When using this product

- do not use otherwise than as directed.
- avoid contact with the eyes, mucous membranes or rashes.
- do not bandage tightly.

Stop use and ask a doctor if

- rash, itching or excessive skin irritation develops.
- conditions worsen.
- symptoms persist for more than 7 days.
- symptoms clear up and occur again within a few days.

Keep out of reach of children.

If swallowed, get medical help or contact a Poison Control Center right away.

Directions

Adults and children 12 years of age and over:

- Clean and dry affected area.
- Shake the can before use.
- Spray onto affected area no longer than 3 seconds.
- Do not use more than 5 times daily for not more than 7 days.

Children under 12 years of age:

- consult a doctor.

Other information

- Do not store in direct sunlight.
- Store in Room Temperature (1 ~ 30 degrees C)

Inactive ingredients

Diphenhydramine, Thymol, Glycol Salycylate, Liquefied petroleum gas, Perfume, Ethyl alcohol, Anhydrous ethanol

Manufactured by:

SINSIN PHARM. CO., LTD.

776-6, Wonsi-Dong, Danwon-Gu, Ansan City, Kyunggi-Do, Korea

http://www.sinsin.com tel: 82-2-2152-4860